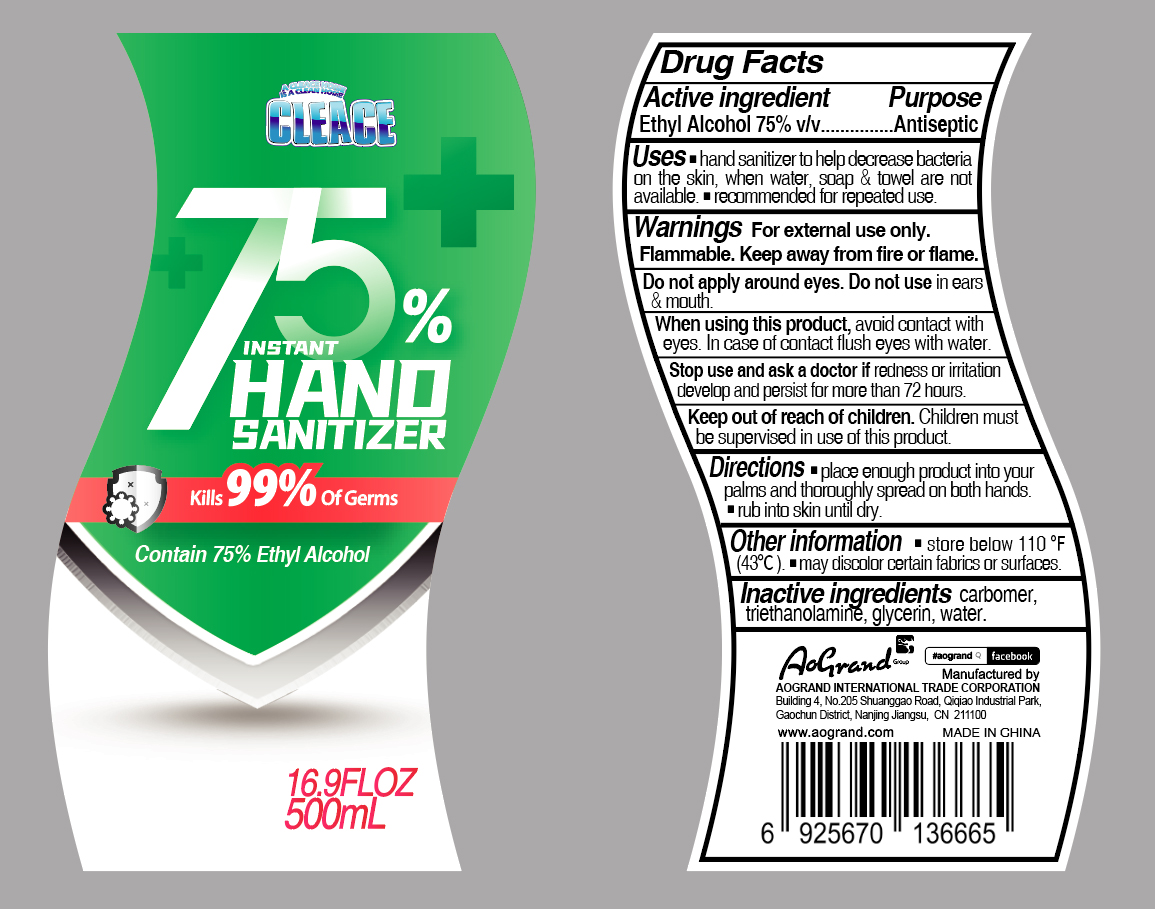 DRUG LABEL: 75% alcohol hand sanitizer
NDC: 75617-001 | Form: GEL
Manufacturer: JASPERS GLOBAL MANUFACTURING INC
Category: otc | Type: HUMAN OTC DRUG LABEL
Date: 20230213

ACTIVE INGREDIENTS: ALCOHOL 7.5 mg/1 mL
INACTIVE INGREDIENTS: ACRYLIC ACID; WATER; TROLAMINE; CARBOMER 940

75% alcohol hand sanitizer

Active ingredient

Alcohol 75% v/v. Purpose: Antiseptic

Purpose

Antiseptic. Hand senitizer

Warnings

For external use only.

Flammable. Keep away from fire or flame.

Do not apply around eyes. Do not use in ears & mouth.

DO NOT USE

Do not apply around eyes. Do not use in ears & mouth.

When using this product, avoid contact with eyes. In case of contact flush eyes with water.

Stop use and ask a doctor if redness or irritation develop and persist for more than 72 hours.

KEEP OUT OF REACH OF CHILDREN.

Children must be supervised in use of this product.

Directions

place enough product into your palms and thoroughly spread on both hands. rub into skin until dry.

OTHER SAFETY INFORMATION

store below 110°F (43°C). may discolor certain fabrics or surfaces.

Inactive ingredients

Carbomer, triethanolamine, glycerin, water

Package Label - Principal Display Panel

500 mL NDC: 75617-001-01